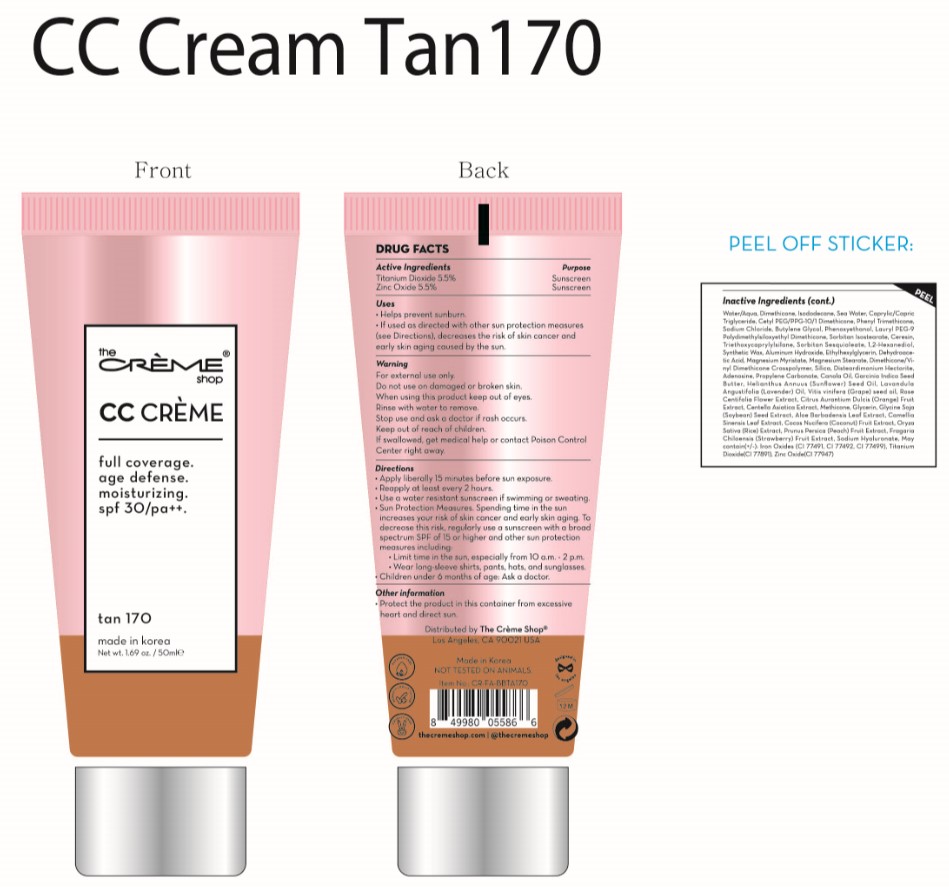 DRUG LABEL: CC Cream Tan170
NDC: 81123-307 | Form: CREAM
Manufacturer: The Creme Shop Inc
Category: otc | Type: HUMAN OTC DRUG LABEL
Date: 20220503

ACTIVE INGREDIENTS: ZINC OXIDE 5.5 mg/100 mL; TITANIUM DIOXIDE 5.5 mg/100 mL
INACTIVE INGREDIENTS: MEDIUM-CHAIN TRIGLYCERIDES; BUTYLENE GLYCOL; SORBITAN ISOSTEARATE; TRIETHOXYCAPRYLYLSILANE; SILICON DIOXIDE; MAGNESIUM STEARATE; DIMETHICONE/VINYL DIMETHICONE CROSSPOLYMER (SOFT PARTICLE); SODIUM CHLORIDE; DIMETHICONE; FERRIC OXIDE RED; LAURYL PEG-9 POLYDIMETHYLSILOXYETHYL DIMETHICONE; BEACH STRAWBERRY; HYALURONATE SODIUM; CETYL PEG/PPG-10/1 DIMETHICONE (HLB 2); FERRIC OXIDE YELLOW; PHENYL TRIMETHICONE; MAGNESIUM MYRISTATE; SORBITAN SESQUIOLEATE; SYNTHETIC WAX (1200 MW); CENTELLA ASIATICA; GREEN TEA LEAF; METHICONE (20 CST); FERROSOFERRIC OXIDE; ETHYLHEXYLGLYCERIN; DISTEARDIMONIUM HECTORITE; ADENOSINE; GARCINIA INDICA SEED BUTTER; SUNFLOWER OIL; ROSA CENTIFOLIA FLOWER; PEACH; SOYBEAN; DEHYDROACETIC ACID; GRAPE SEED OIL; LAVENDER OIL; ORANGE; GLYCERIN; ALOE VERA LEAF; COCONUT; RICE GERM; PROPYLENE CARBONATE; PHENOXYETHANOL; CERESIN; 1,2-HEXANEDIOL; CANOLA OIL; ALUMINUM HYDROXIDE; WATER; ISODODECANE

81123-307 Tan170

Active Ingredient

Titanium Dioxide 5.5%
Zinc Oxide 5.5%

Purpose

Helps prevent sunburn.

Uses

If uses as directed with other sun protection measures(see Directions), decreases the risk of skin cancer and early skin aging caused by the sun.

Warnings

For external use only.
Rinse with water to remove.
If swallowed, get medical help or contact Poison Control Center right away.

Warnings

Do not use on damaged or broken skin.

Warnings

Keep out of reach of children.

Warnings

Stop use and ask a doctor if rash occurs.

Directions

Apply liberally 15 minutes before sun exposure.
Reapply at least every 2 hours.
Use a water resistant sunscreen if swimming or sweating.
Sun Protection Measures. Spending time in the sun increases your risk of skin cancer and early skin aging. To decrease this risk, regularly use a sunscreen with a broad spectrum SPF of 15 of higher and other sun protection measures including:
Limit time in the sun, especially from 10 a.m. - 2 p.m.
Wear long-sleeve shirts, pants, hats, and sunglasses.
Children under 6months of age: Ask a doctor.

Other Information

Protect the product in this container from excessive heart and direct sun.

Inactive Ingredient

Water, Sea Water, Dimethicone, Isododecane, Iron Oxide Yellow, Caprylic/Capric Triglyceride, Cetyl PEG/PPG-10/1 Dimethicone, Phenyl Trimethicone, Iron Oxide Red, Sodium Chloride, Butylene Glycol, Lauryl PEG-9 Polydimethylsiloxyethyl Dimethicone, Iron Oxide Black, Phenoxyethanol, Sorbitan Isostearate, Triethoxycaprylylsilane, Ceresin, Silica, Magnesium Myristate, Magnesium Stearate, Sorbitan Sesquioleate, 1,2-Hexanediol, Synthetic Wax, Dimethicone/Vinyl Dimethicone Crosspolymer, Aluminum Hydroxide, Ethylhexylglycerin, Dehydroacetic Acid, Disteardimonium Hectorite, Methicone, Adenosine, Propylene Carbonate, Canola Oil, Garcinia Indica Seed Butter, Helianthus Annuus (Sunflower) Seed Oil, Lavandula Angustifolia (Lavender) Oil, Vitis vinifera (Grape) seed oil, Rose Centifolia Flower Extract, Citrus Aurantium Dulcis (Orange) Fruit Extract, Centella Asiatica Extract, Glycerin, Glycine Soja (Soybean) Seed Extract, Aloe Barbadensis Leaf Extract, Camellia Sinensis Leaf Extract, Cocos Nucifera (Coconut) Fruit Extract, Oryza Sativa (Rice) Extract, Prunus Persica (Peach) Fruit Extract, Fragaria Chiloensis (Strawberry) Fruit Extract, Sodium Hyaluronate